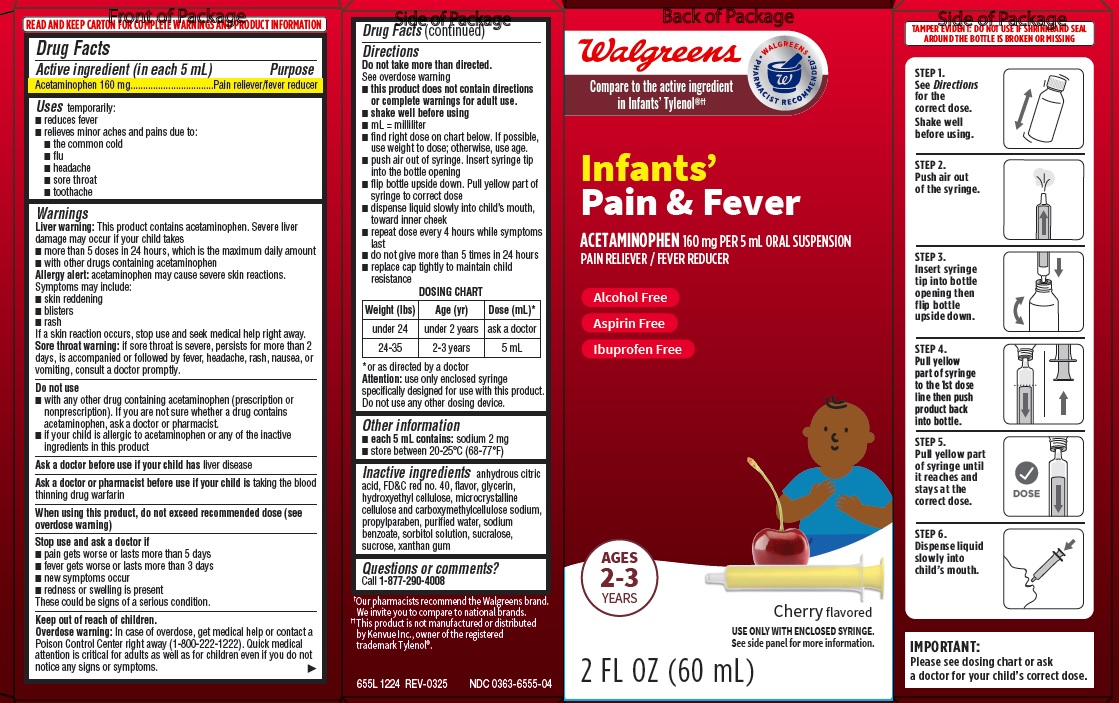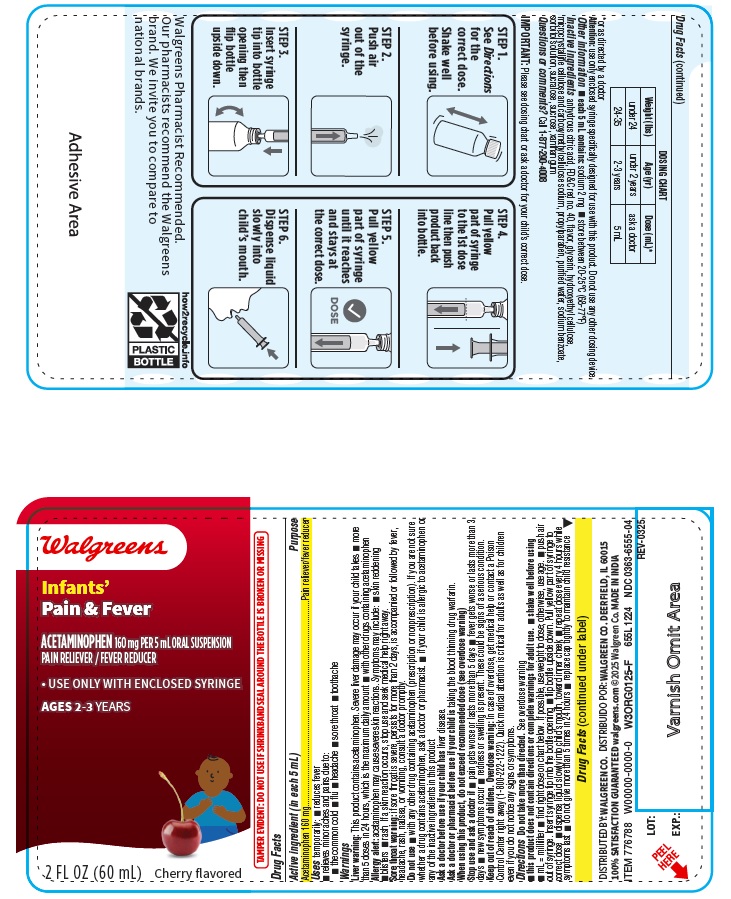 DRUG LABEL: Infants Pain and Fever
NDC: 0363-6555 | Form: SUSPENSION
Manufacturer: WALGREENS
Category: otc | Type: HUMAN OTC DRUG LABEL
Date: 20250328

ACTIVE INGREDIENTS: ACETAMINOPHEN 160 mg/5 mL
INACTIVE INGREDIENTS: GLYCERIN; SUCRALOSE; FD&C RED NO. 40; SUCROSE; SORBITOL SOLUTION; WATER; HYDROXYETHYL CELLULOSE, UNSPECIFIED; CARBOXYMETHYLCELLULOSE SODIUM, UNSPECIFIED FORM; SODIUM BENZOATE; XANTHAN GUM; ANHYDROUS CITRIC ACID; PROPYLPARABEN; MICROCRYSTALLINE CELLULOSE

655L Walgreens Acetaminophen 160 mg suspension Infants

Active ingredient (in each 5 mL)
Acetaminophen 160 mg

Purpose
Pain reliever/fever reducer

INDICATIONS AND USAGE

Uses temporarily:
■ reduces fever
■ relieves minor aches and pains due to:
- the common cold
- flu
- headache
- sore throat
- toothache

Warnings
Liver warning: This product contains acetaminophen. Severe liver damage may occur if your child takes
■ more than 5 doses in 24 hours, which is the maximum daily amount
■ with other drugs containing acetaminophen
Allergy alert: acetaminophen may cause severe skin reactions. Symptoms may include:
■ skin reddening
■ blisters
■ rash
If a skin reaction occurs, stop use and seek medical help right away.
Sore throat warning: if sore throat is severe, persists for more than 2 days, is accompanied or followed by fever, headache, rash, nausea, or vomiting, consult a doctor promptly.

Do not use
■ with any other drug containing acetaminophen (prescription or nonprescription). If you are not sure whether a drug contains acetaminophen, ask a doctor or pharmacist.
■ if your child is allergic to acetaminophen or any of the inactive ingredients in this product

Ask a doctor before use if your child has liver disease

Ask a doctor or pharmacist before use if your child is taking the blood thinning drug warfarin

When using this product, do not exceed recommended dose (see overdose warning)

Stop use and ask a doctor if
■ pain gets worse or lasts more than 5 days
■ fever gets worse or lasts more than 3 days
■ new symptoms occur
■ redness or swelling is present
These could be signs of a serious condition.

Keep out of reach of children.
Overdose warning: In case of overdose, get medical help or contact a Poison Control Center right away (1-800-222-1222). Quick medical attention is critical for adults as well as for children even if you do not notice any signs or symptoms.

Directions
Do not take more than directed.
See overdose warning
■ this product does not contain directions or complete warnings for adult use.
■ shake well before using
■ mL = milliliter
■ find right dose on chart below. If possible, use weight to dose; otherwise, use age.
■ push air out of syringe. Insert syringe tip into the bottle opening
■ flip bottle upside down. Pull yellow part of syringe to correct dose
■ dispense liquid slowly into child’s mouth, toward inner cheek
■ repeat dose every 4 hours while symptoms last
■ do not give more than 5 times in 24 hours
■ replace cap tightly to maintain child
resistance

DOSING CHART

Weight (lbs) | Age (yr) | Dose (mL)*
under 24 | under 2 years | ask a doctor
24-35 | 2-3 years | 5 mL

*or as directed by a doctor

Attention: use only enclosed syringe specifically designed for use with this product.
Do not use any other dosing device.

Other information
■ each 5 mL contains: sodium 2 mg
■ store between 20-25°C (68-77°F)

INACTIVE INGREDIENT

Inactive ingredients anhydrous citric acid, FD&C red no. 40, flavor, glycerin, hydroxyethyl cellulose, microcrystalline cellulose and carboxymethylcellulose sodium, propylparaben, purified water, sodium benzoate, sorbitol solution, sucralose, sucrose, xanthan gum

Questions or comments?
Call 1-877-290-4008